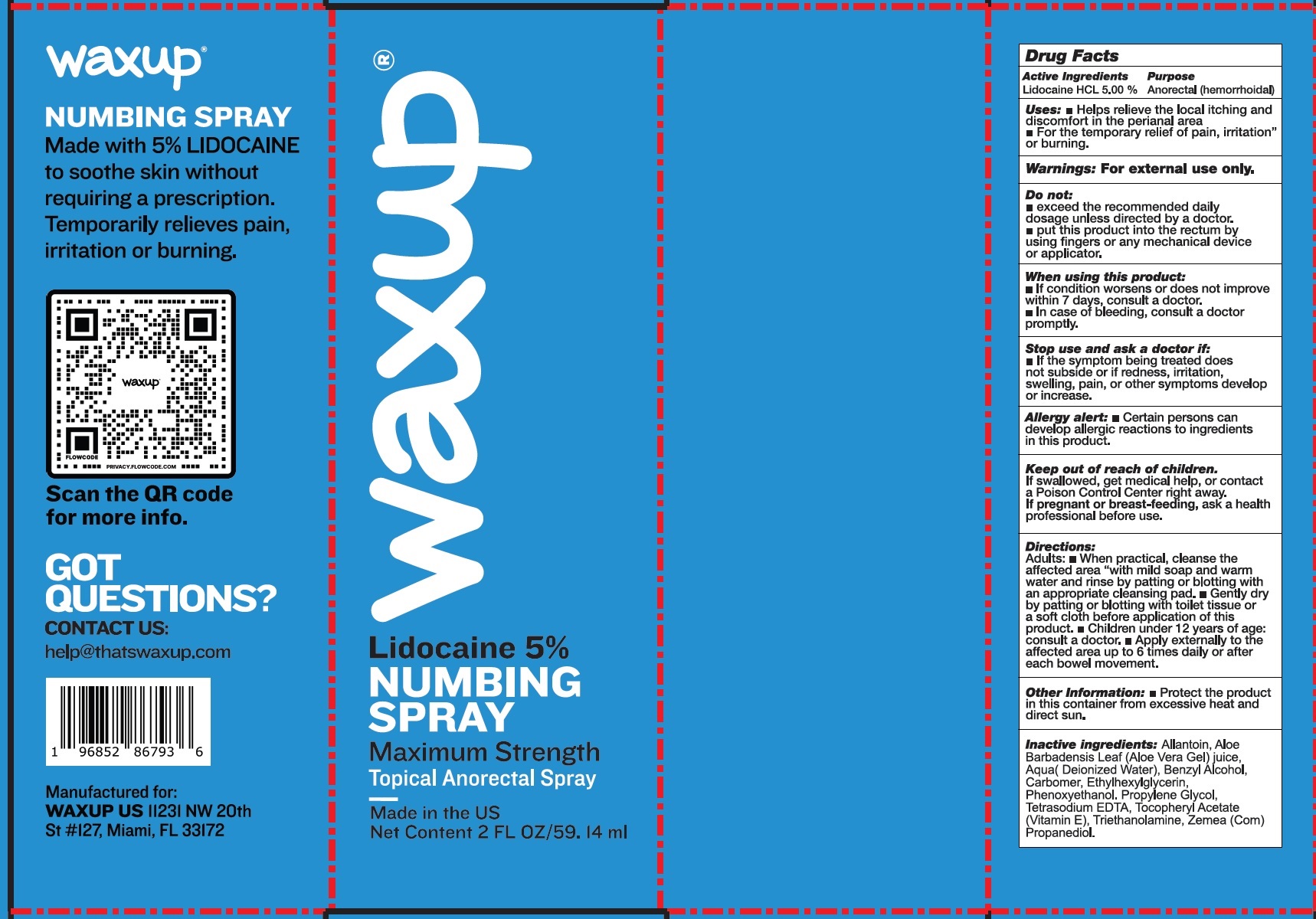 DRUG LABEL: WAXUP Numbing
NDC: 83163-386 | Form: LIQUID
Manufacturer: CONSTRUSOLUTION, LLC
Category: otc | Type: HUMAN OTC DRUG LABEL
Date: 20231106

ACTIVE INGREDIENTS: LIDOCAINE HYDROCHLORIDE 50 mg/1 mL
INACTIVE INGREDIENTS: ALLANTOIN; ALOE VERA LEAF; WATER; BENZYL ALCOHOL; CARBOMER HOMOPOLYMER, UNSPECIFIED TYPE; ETHYLHEXYLGLYCERIN; PHENOXYETHANOL; PROPYLENE GLYCOL; EDETATE SODIUM; .ALPHA.-TOCOPHEROL ACETATE; TROLAMINE; CORN

WAXUP Numbing Spray

Active Ingredients

Lidocaine HCL 5.00%

Purpose

Anorectal (hemorrhoidal)

Uses:

- Helps relieve the local itching and discomfort in the perianal area
- For the temporary relief of pain, irritation or burning.

Warnings:

For external use only.

Do not:

- exceed the recommended daily dosage unless directed by a doctor.
- put this product into the rectum by using fingers or any mechanical device or applicator.

When using this product:

- If condition worsens or does not improve within 7 days, consult a doctor.
- In case of bleeding, consult a doctor promptly.

Stop use and ask a doctor if:

- If the symptom being treated does not subside or if redness, irritation, swelling, pain, or other symptoms develop or increase.

- Certain persons can develop allergic reactions to ingredients in this product.

Allergy alert:

Keep out of raech of children.

If swallowed, get medical help, or contact a Poison Control Center right away.

If pregnant or breast-feeding,

ask a health professional before use.

Directions:

Adults:• When practical, cleanse the affected area "with mild soap and warm water and rinse by patting or blotting with an appropriate cleansing pad. • Gently dry by patting or blotting with toilet tissue or a soft cloth before application of this product. • Children under 12 years of age: consult a doctor. • Apply externally to the affected area up to 6 times daily or after each bowel movement.

Other Information:

- Protect the product in this container from excessive heat and direct sun.

Inactive ingredients:

Allantoin, Aloe Barbadensis Leaf (Aloe Vera Gel) Juice, Aqua (Deionized Water), Benzyl Alcohol, Carbomer, Ethylhexylglycerin, Phenoxyethanol, Propylene Glycol, Tetrasodium EDTA, Tocopheryl Acetate (Vitamin E), Triethanolamine, Zemea (Corn) Propanediol.